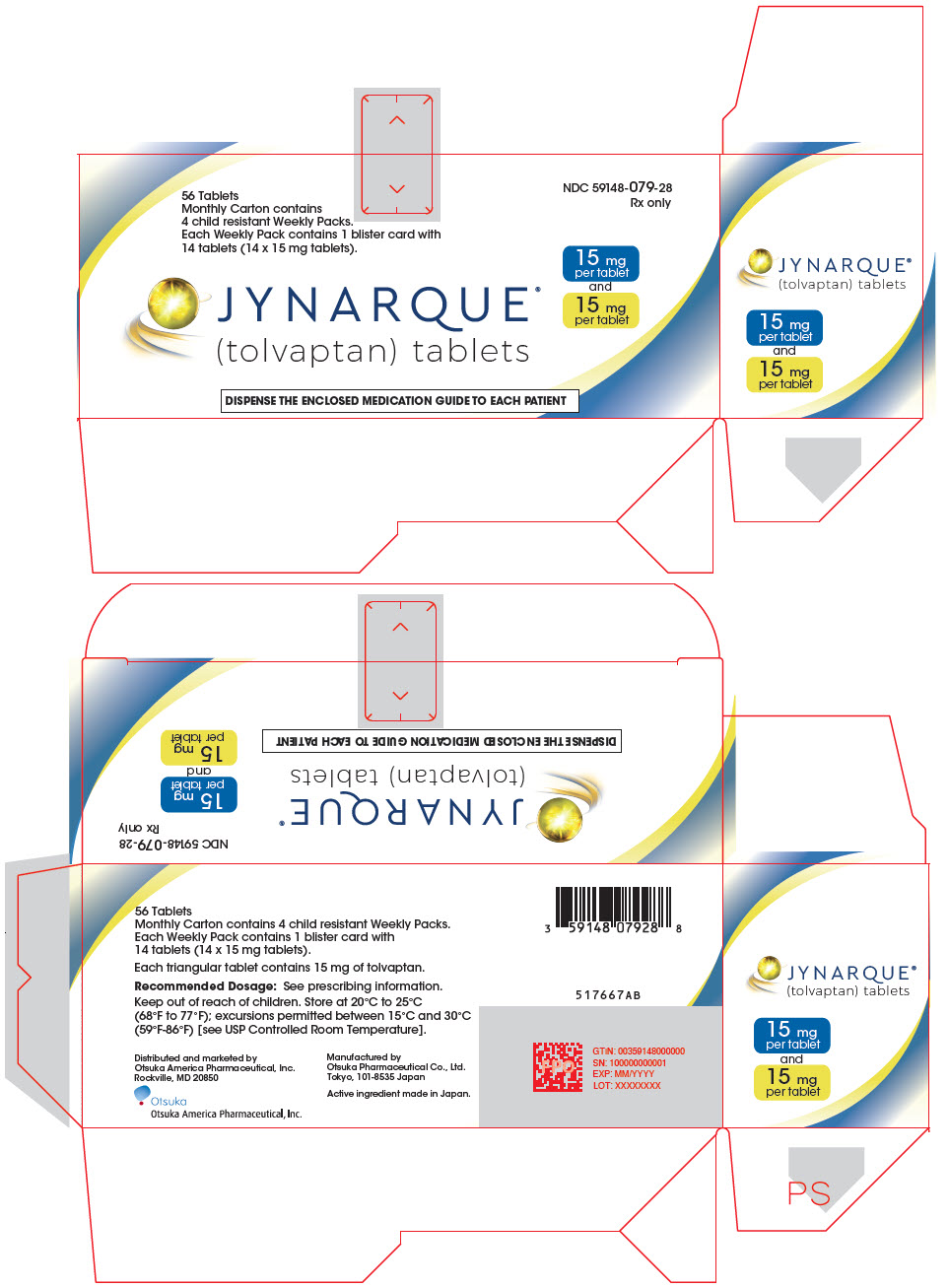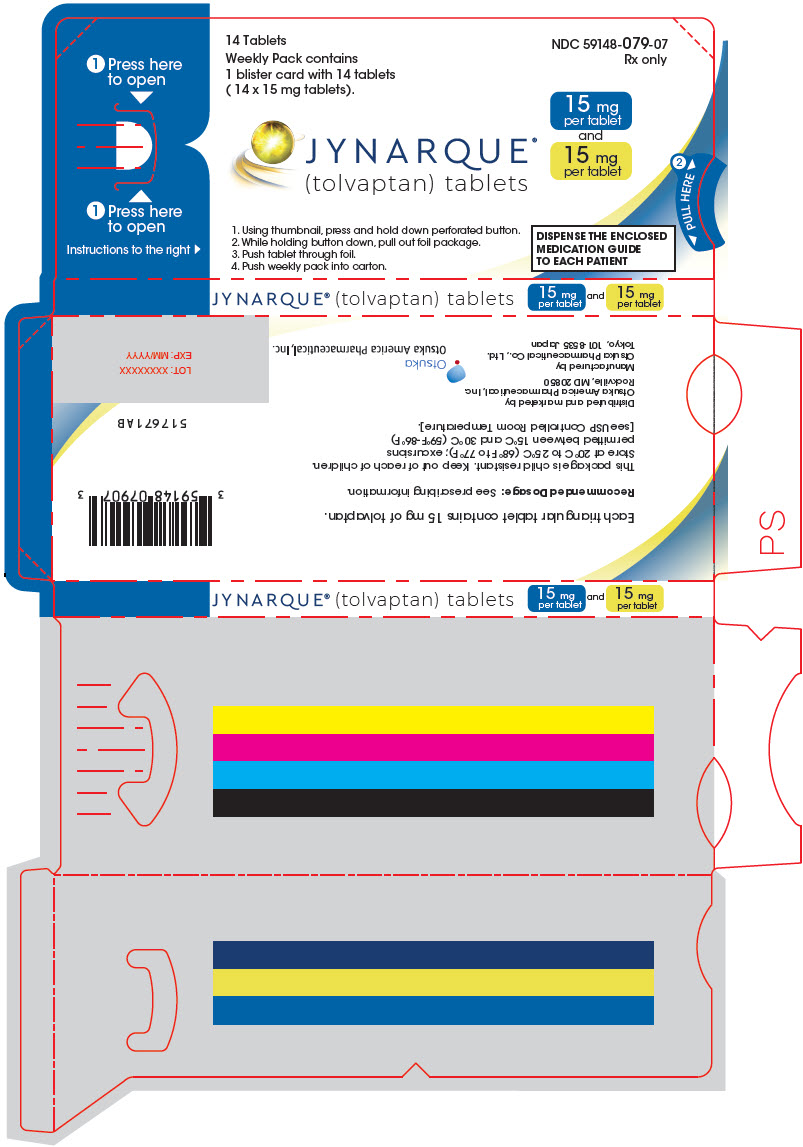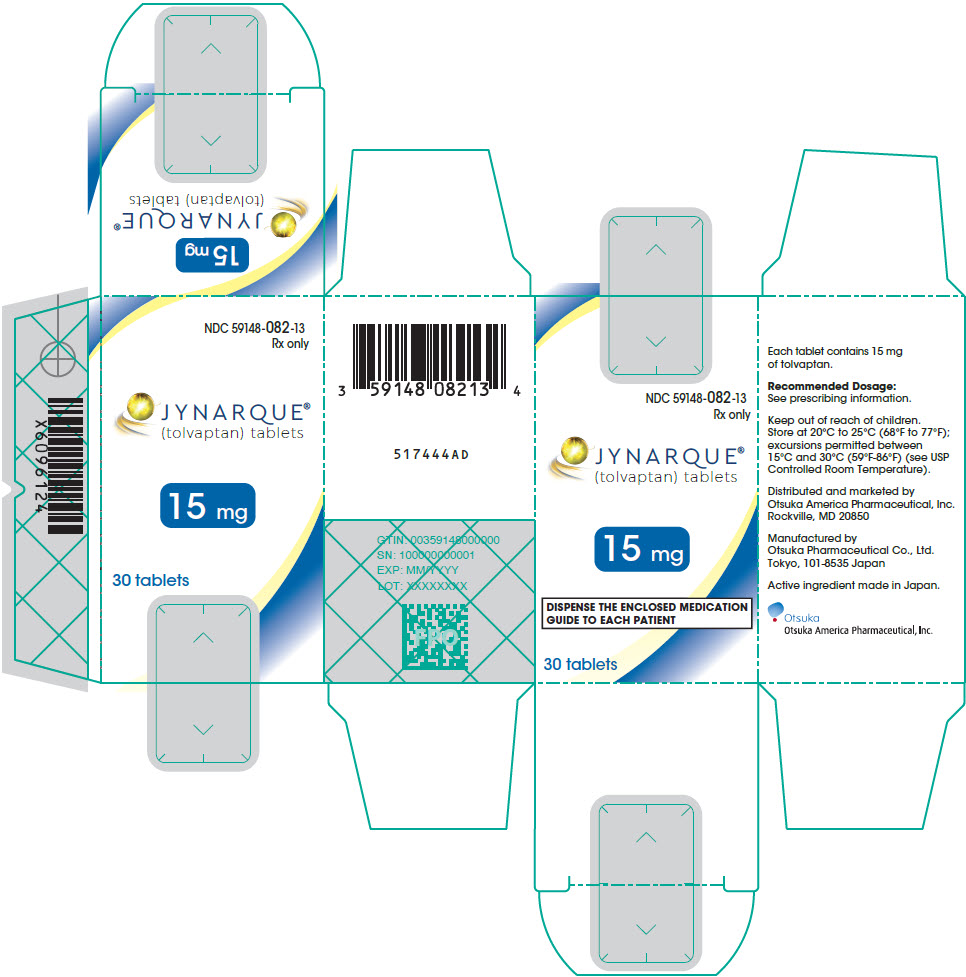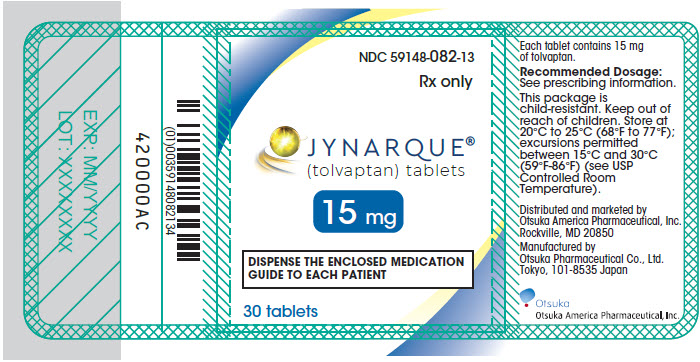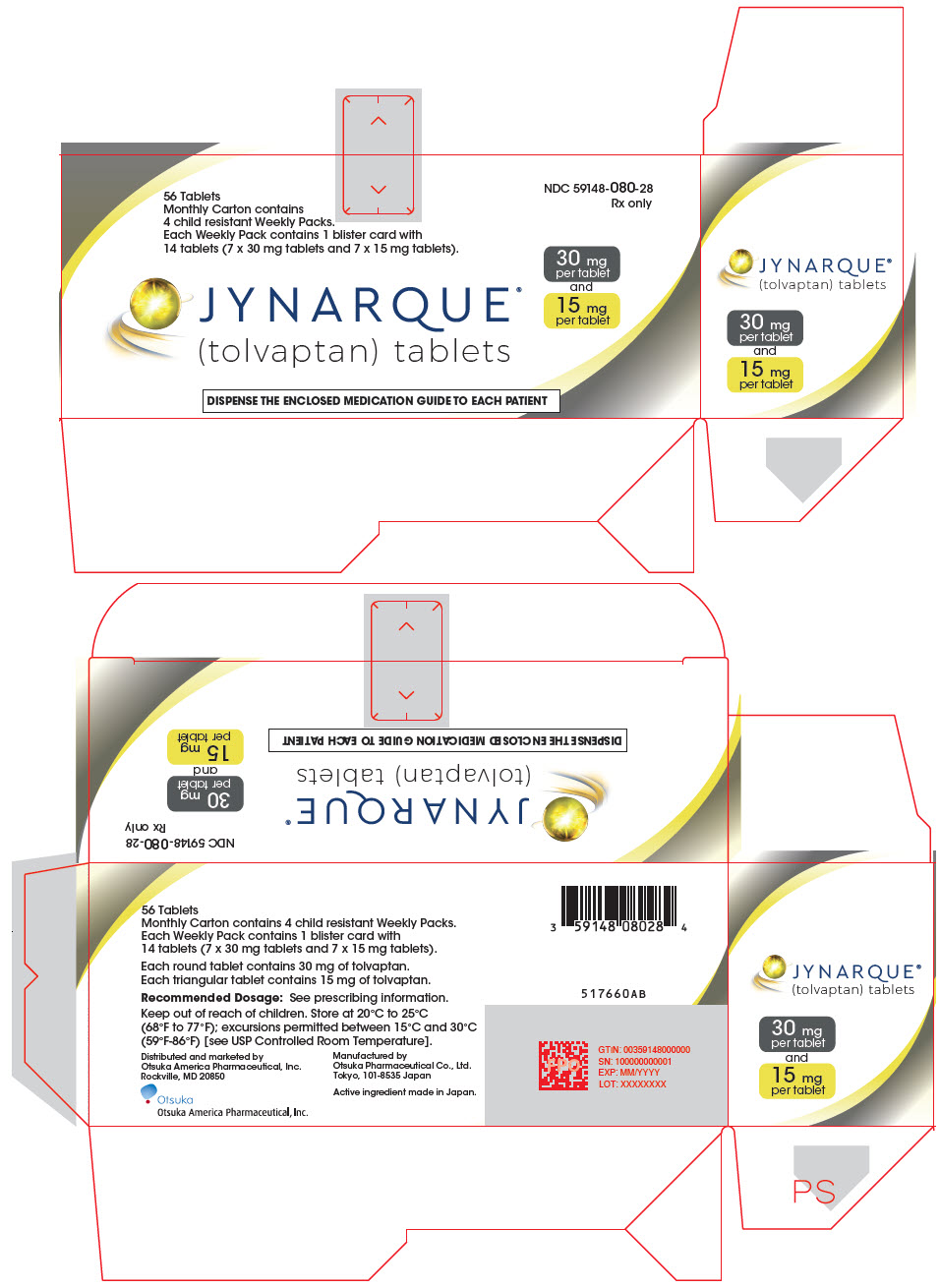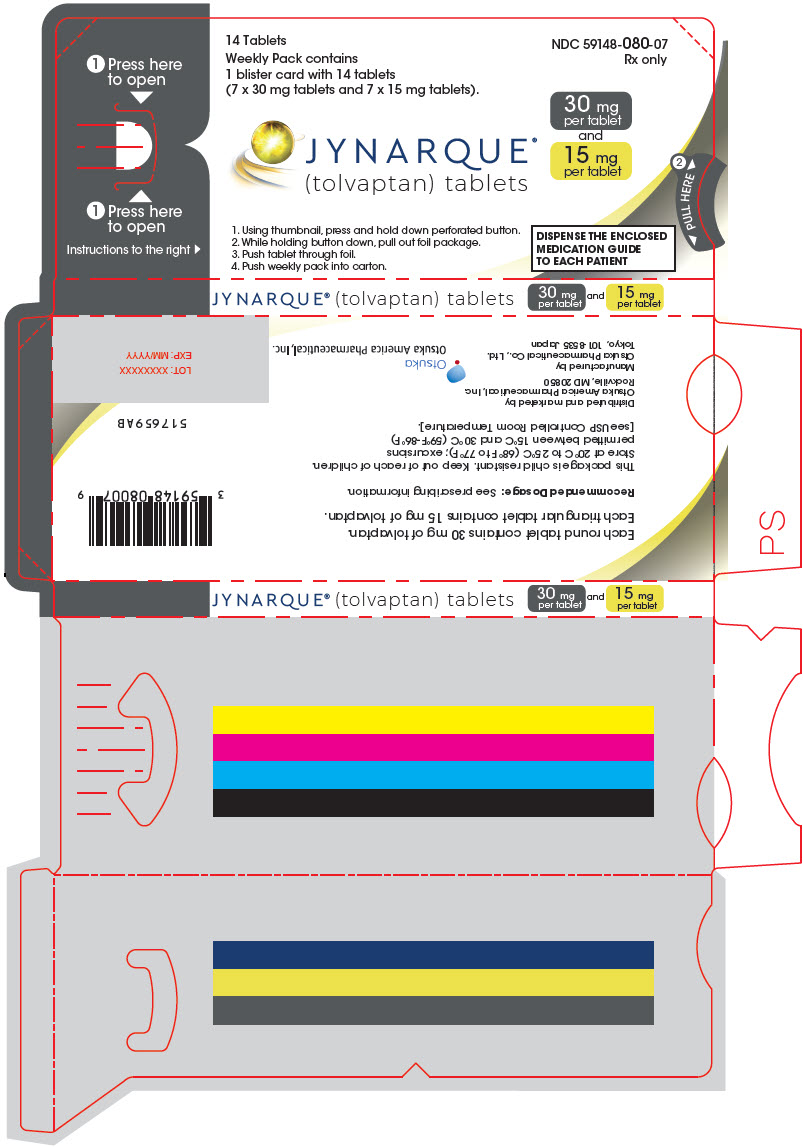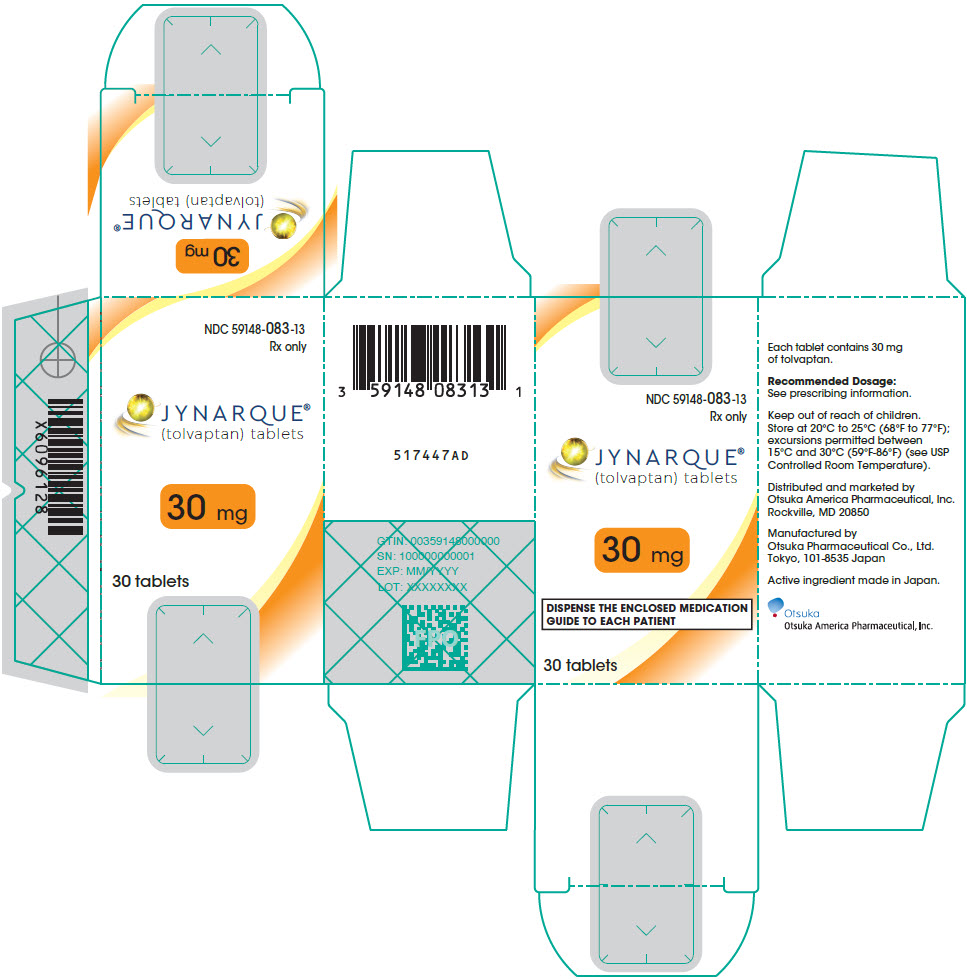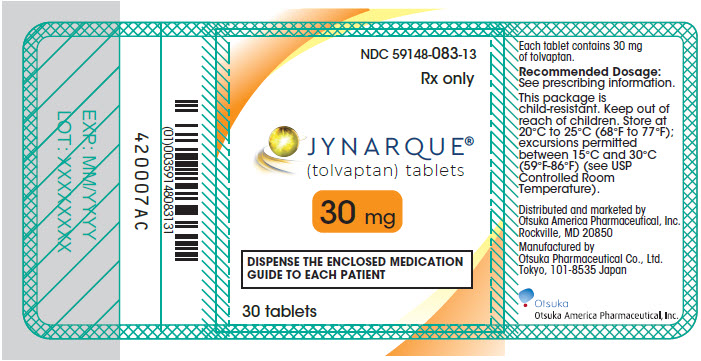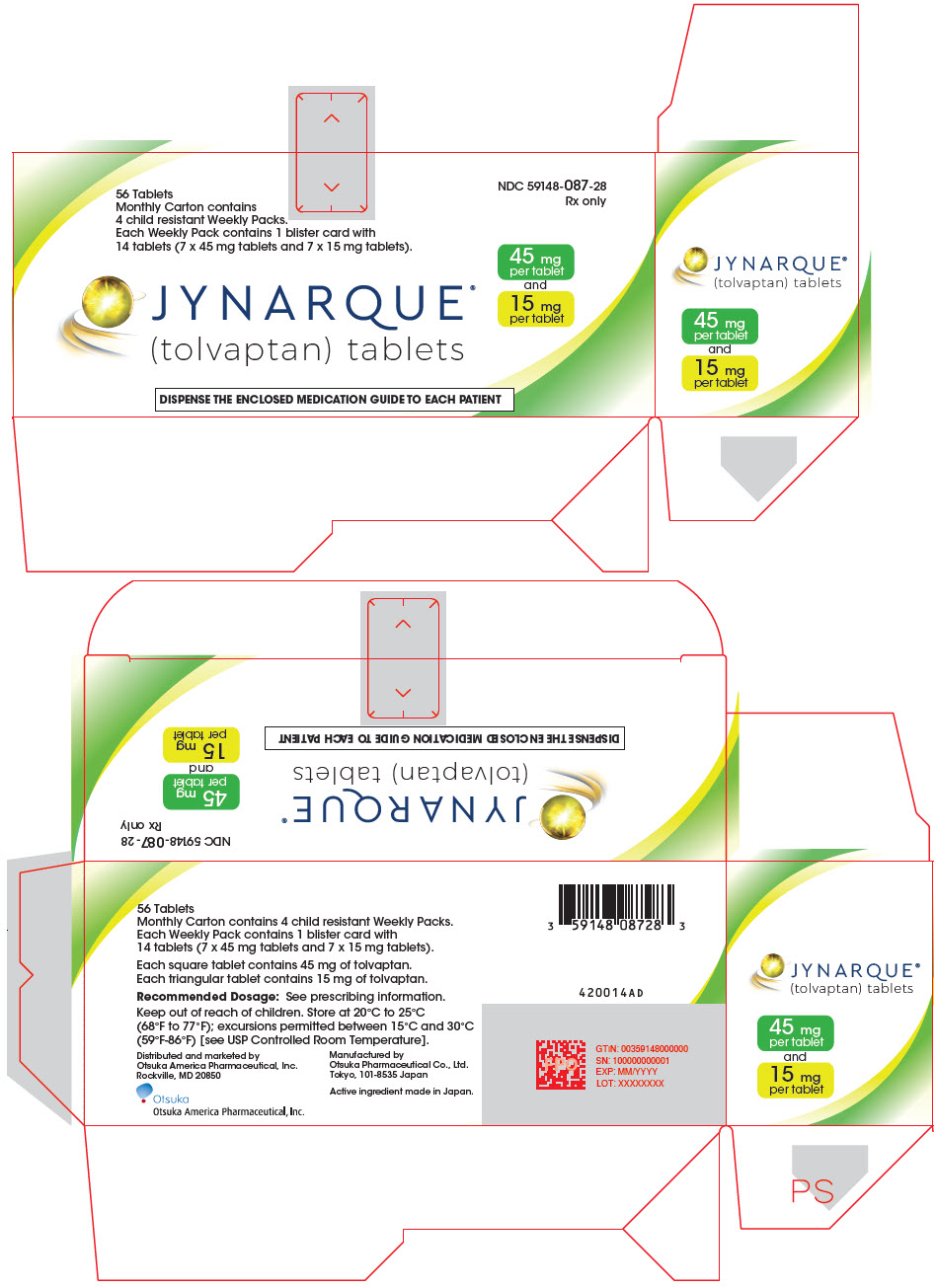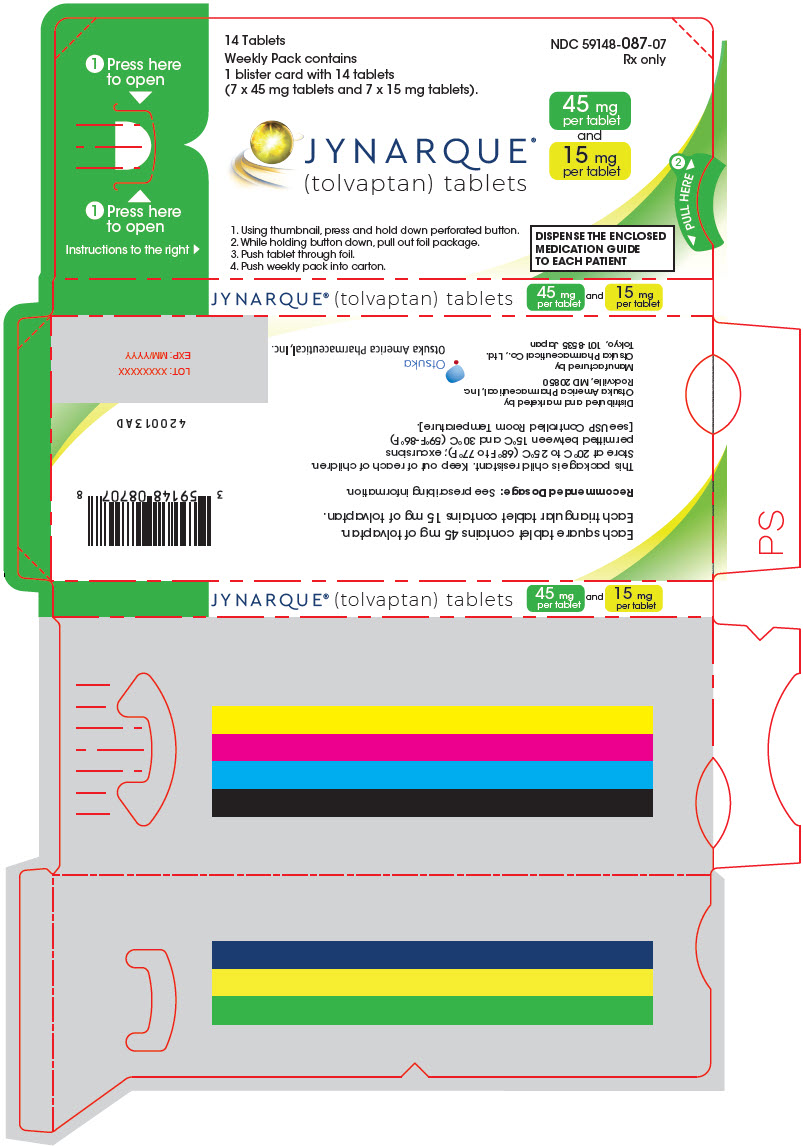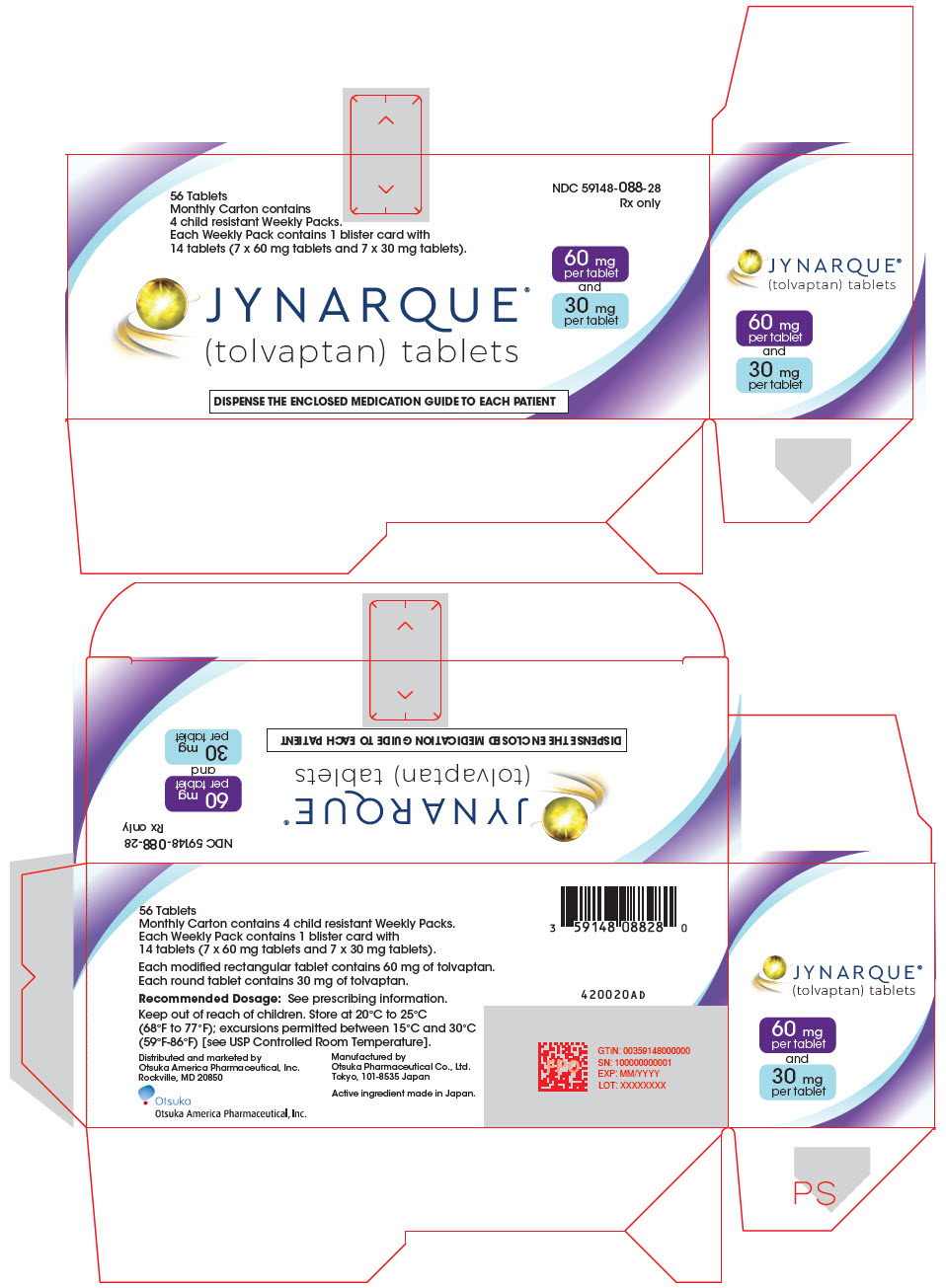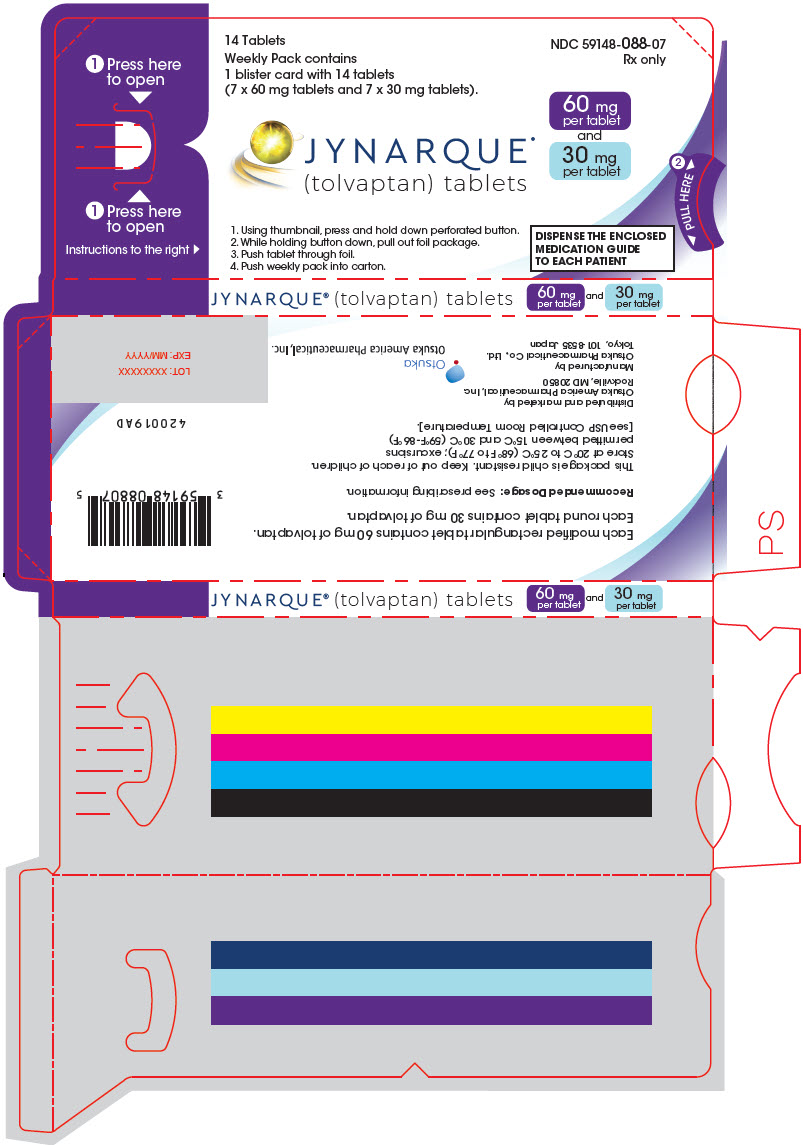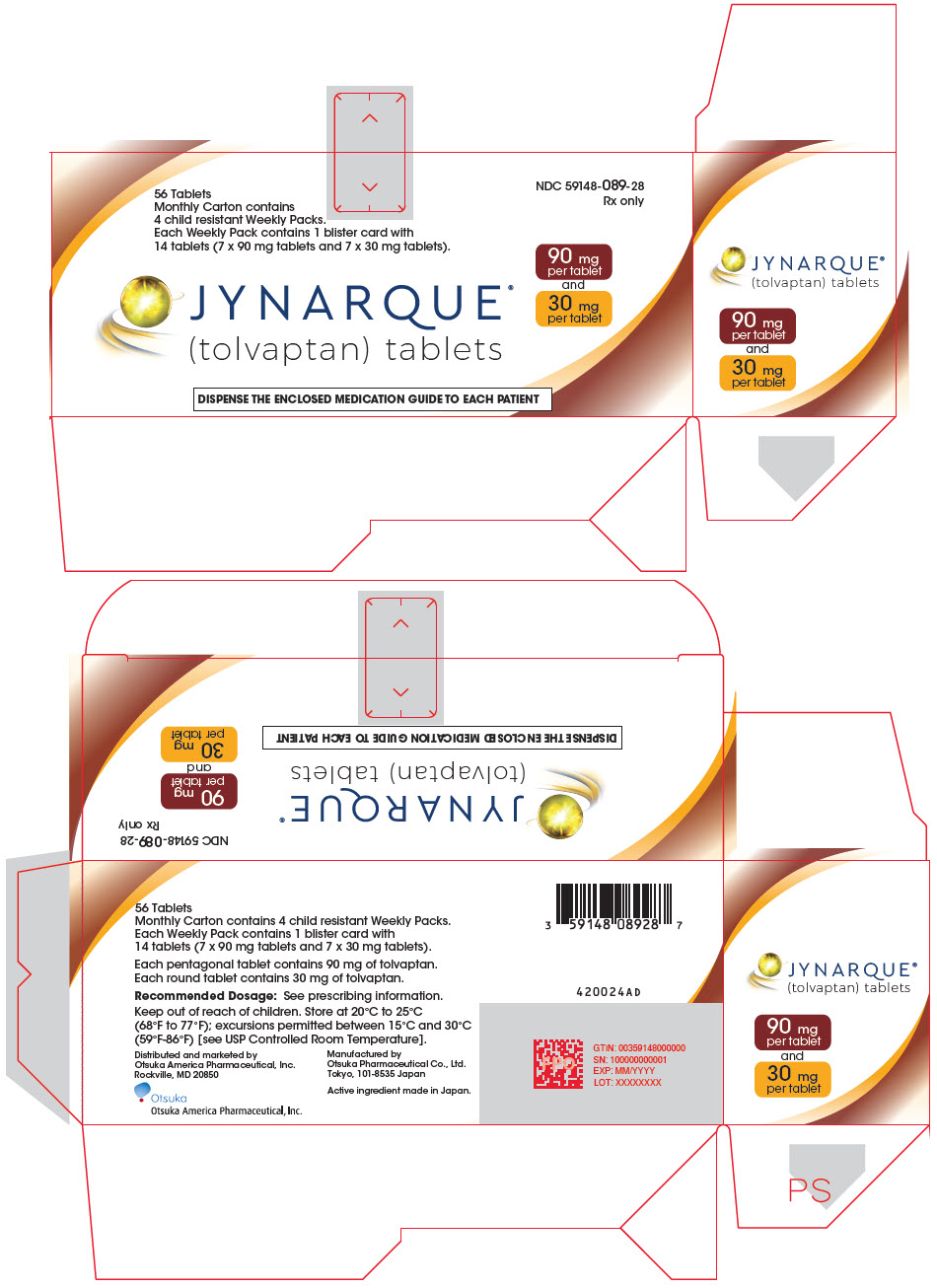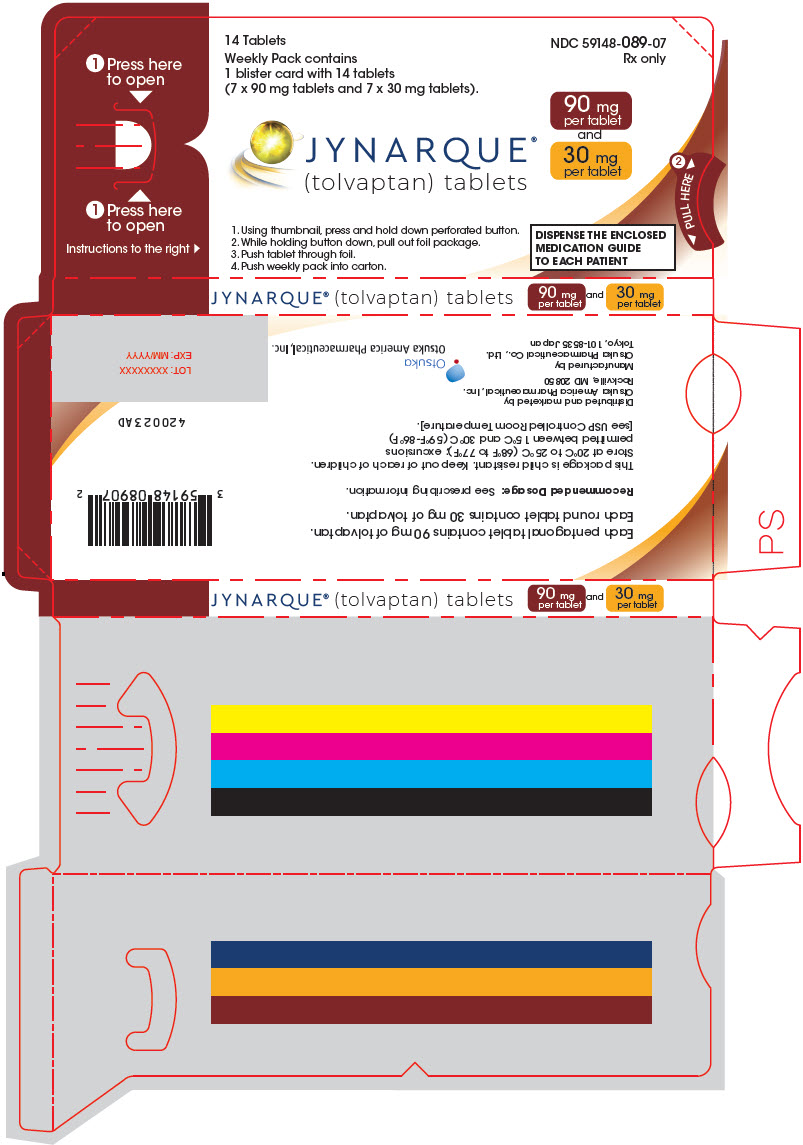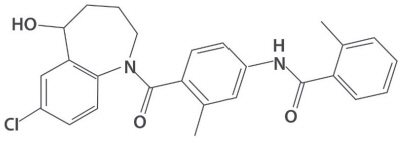 DRUG LABEL: Jynarque
NDC: 59148-079 | Form: KIT | Route: ORAL
Manufacturer: Otsuka America Pharmaceutical, Inc.
Category: prescription | Type: HUMAN PRESCRIPTION DRUG LABEL
Date: 20251106

ACTIVE INGREDIENTS: TOLVAPTAN 15 mg/1 1; TOLVAPTAN 15 mg/1 1
INACTIVE INGREDIENTS: STARCH, CORN; HYDROXYPROPYL CELLULOSE, UNSPECIFIED; LACTOSE MONOHYDRATE; LOW-SUBSTITUTED HYDROXYPROPYL CELLULOSE, UNSPECIFIED; MAGNESIUM STEARATE; MICROCRYSTALLINE CELLULOSE; FD&C BLUE NO. 2 ALUMINUM LAKE; STARCH, CORN; HYDROXYPROPYL CELLULOSE, UNSPECIFIED; LACTOSE MONOHYDRATE; LOW-SUBSTITUTED HYDROXYPROPYL CELLULOSE, UNSPECIFIED; MAGNESIUM STEARATE; MICROCRYSTALLINE CELLULOSE; FD&C BLUE NO. 2 ALUMINUM LAKE

HIGHLIGHTS OF PRESCRIBING INFORMATION

These highlights do not include all the information needed to use JYNARQUE safely and effectively. See full prescribing information for JYNARQUE.
JYNARQUE® (tolvaptan) tablets, for oral use
Initial U.S. Approval: 2009

WARNING: RISK OF SERIOUS LIVER INJURY

See full prescribing information for complete boxed warning.

- JYNARQUE (tolvaptan) can cause serious and potentially fatal liver injury. Acute liver failure requiring liver transplantation has been reported (5.1)
- Measure transaminases and bilirubin before initiating treatment, at 2 weeks and 4 weeks after initiation, then continuing monthly for the first 18 months and every 3 months thereafter (5.1)
- JYNARQUE is available only through a restricted distribution program called the Tolvaptan for ADPKD Shared System REMS (5.2)

RECENT MAJOR CHANGES

Warnings and Precautions Tolvaptan for ADPKD Shared System REMS (5.2) | 3/2025

1 INDICATIONS AND USAGE

JYNARQUE is a selective vasopressin V2-receptor antagonist indicated to slow kidney function decline in adults at risk of rapidly progressing autosomal dominant polycystic kidney disease (ADPKD) (1)

2 DOSAGE AND ADMINISTRATION

- Recommended dosage (2.1)
  Initial Dosage |  | Titration Step |  | Target Dosage
  1st Dose | 45 mg | 1st Dose | 60 mg | 1st Dose | 90 mg
  2nd Dose (8 hours later) | 15 mg | 2nd Dose (8 hours later) | 30 mg | 2nd Dose (8 hours later) | 30 mg
  Total Daily Dose | 60 mg | Total Daily Dose | 90 mg | Total Daily Dose | 120 mg

- Dose adjustment is recommended for patients taking moderate CYP3A inhibitors (2.4, 5.4, 7.1)

3 DOSAGE FORMS AND STRENGTHS

- Tablets: 15 mg, 30 mg, 45 mg, 60 mg and 90 mg (3)

4 CONTRAINDICATIONS

- History of signs or symptoms of significant liver impairment or injury, does not include uncomplicated polycystic liver disease (4)
- Concomitant use of strong CYP3A inhibitors is contraindicated (4)
- Uncorrected abnormal blood sodium concentrations (4, 5.3)
- Unable to sense or respond to thirst (4)
- Hypovolemia (4)
- Hypersensitivity to tolvaptan or any of its components (4)
- Uncorrected urinary outflow obstruction (4)
- Anuria (4)

5 WARNINGS AND PRECAUTIONS

- Hypernatremia, dehydration and hypovolemia: May require intervention (5.3)

6 ADVERSE REACTIONS

Most common observed adverse reactions with JYNARQUE (incidence >10% and at least twice that for placebo) were thirst, polyuria, nocturia, pollakiuria and polydipsia (6.1)

To report SUSPECTED ADVERSE REACTIONS, contact Otsuka America Pharmaceutical, Inc. at 1-800-438-9927 or FDA at 1-800-FDA-1088 or www.fda.gov/medwatch.

7 DRUG INTERACTIONS

Avoid concomitant use with:

- Strong CYP3A Inducers (7.1)
- V2-Receptor Agonists (7.2)

8 USE IN SPECIFIC POPULATIONS

- Pregnancy: May cause fetal harm (8.1)
- Lactation: Breastfeeding not recommended (8.2)

FULL PRESCRIBING INFORMATION

WARNING: RISK OF SERIOUS LIVER INJURY

JYNARQUE (tolvaptan) can cause serious and potentially fatal liver injury. Acute liver failure requiring liver transplantation has been reported [see Warnings and Precautions (5.1)].

Measure ALT, AST and bilirubin before initiating treatment, at 2 weeks and 4 weeks after initiation, then monthly for the first 18 months and every 3 months thereafter [see Warnings and Precautions (5.1)]. Prompt action in response to laboratory abnormalities, signs, or symptoms indicative of hepatic injury can mitigate, but not eliminate, the risk of serious hepatotoxicity.

Because of the risks of serious liver injury, JYNARQUE is available only through a restricted distribution program under a Risk Evaluation and Mitigation Strategy (REMS) called the Tolvaptan for ADPKD Shared System REMS [see Warnings and Precautions (5.2)].

1 INDICATIONS AND USAGE

JYNARQUE is indicated to slow kidney function decline in adults at risk of rapidly progressing autosomal dominant polycystic kidney disease (ADPKD).

2 DOSAGE AND ADMINISTRATION

2.1 Recommended Dosage

The initial dosage for JYNARQUE is 60 mg orally per day as 45 mg taken on waking and 15 mg taken 8 hours later. Titrate to 60 mg plus 30 mg then to 90 mg plus 30 mg per day if tolerated with at least weekly intervals between titrations. Patients may down-titrate based on tolerability. Encourage patients to drink enough water to avoid thirst or dehydration.

2.2 Monitoring

To mitigate the risk of significant or irreversible liver injury, perform blood testing for ALT, AST and bilirubin prior to initiation of JYNARQUE, at 2 and 4 weeks after initiation, monthly for 18 months and every 3 months thereafter. Monitor for concurrent symptoms that may indicate liver injury [see Warnings and Precautions (5.1)].

2.3 Missed Doses

If a dose of JYNARQUE is not taken at the scheduled time, take the next dose at its scheduled time.

2.4 Co-Administration with CYP3A Inhibitors

CYP3A Inhibitors

Concomitant use of strong CYP3A inhibitors is contraindicated [see Contraindications (4) and Warnings and Precautions (5.4)].

In patients taking concomitant moderate CYP3A inhibitors, reduce the dose of JYNARQUE per Table 1. Consider further reductions if patients cannot tolerate the reduced dose [see Warnings and Precautions (5.4) and Drug Interactions (7.1)]. Interrupt JYNARQUE temporarily for short term therapy with moderate CYP3A inhibitors if the recommended reduced doses are not available.

Table 1: Dose adjustment for patients taking moderate CYP3A inhibitors
Standard Morning and Afternoon Dose (mg) | Dose (mg) with Moderate CYP3A Inhibitors
90 mg and 30 mg | 45 mg and 15 mg
60 mg and 30 mg | 30 mg and 15 mg
45 mg and 15 mg | 15 mg and 15 mg

3 DOSAGE FORMS AND STRENGTHS

JYNARQUE (tolvaptan) is supplied as non-scored, blue, shallow-convex, immediate release tablets, debossed with "OTSUKA" and the tablet strength (mg) on one side as follows:

Strength | Shape
15 mg | triangular
30 mg | round
45 mg | square
60 mg | rectangular
90 mg | pentagonal

4 CONTRAINDICATIONS

JYNARQUE is contraindicated in patients:

- With a history, signs or symptoms of significant liver impairment or injury. This contraindication does not apply to uncomplicated polycystic liver disease [see Warnings and Precautions (5.1)]
- Taking strong CYP3A inhibitors
- With uncorrected abnormal blood sodium concentrations [see Warnings and Precautions (5.3)]
- Unable to sense or respond to thirst [see Warnings and Precautions (5.3)]
- Hypovolemia [see Warnings and Precautions (5.3)]
- Hypersensitivity (e.g., anaphylaxis, rash) to tolvaptan or any component of the product [see Adverse Reactions (6)]
- Uncorrected urinary outflow obstruction
- Anuria

5 WARNINGS AND PRECAUTIONS

5.1 Serious Liver Injury

JYNARQUE can cause serious and potentially fatal liver injury. Acute liver failure requiring liver transplantation has been reported in the post-marketing ADPKD experience. Discontinuation in response to laboratory abnormalities or signs or symptoms of liver injury (such as fatigue, anorexia, nausea, right upper abdominal discomfort, vomiting, fever, rash, pruritus, icterus, dark urine or jaundice) can reduce the risk of severe hepatotoxicity.

In a 3-year placebo-controlled trial and its open-label extension (in which patients' liver tests were monitored every 4 months), evidence of serious hepatocellular injury (elevations of hepatic transaminases of at least 3 times the upper limit of normal [ULN] combined with elevated bilirubin at least 2 times the ULN) occurred in 0.2% (3/1487) of tolvaptan-treated patients compared to none of the placebo-treated patients.

To reduce the risk of significant or irreversible liver injury, assess ALT, AST and bilirubin prior to initiation of JYNARQUE, at 2 weeks and 4 weeks after initiation, then monthly for 18 months and every 3 months thereafter.

At the onset of signs or symptoms consistent with hepatic injury or if ALT, AST, or bilirubin increase to >2 times ULN, immediately discontinue JYNARQUE, obtain repeat tests as soon as possible (within 48 to 72 hours), and continue testing as appropriate. If laboratory abnormalities stabilize or resolve, JYNARQUE may be reinitiated with increased frequency of monitoring as long as ALT and AST remain below 3 times the ULN.

Do not restart JYNARQUE in patients who experience signs or symptoms consistent with hepatic injury or whose ALT or AST ever exceeds 3 times the ULN during treatment with tolvaptan, unless there is another explanation for liver injury and the injury has resolved.

In patients with a stable, low baseline AST or ALT, an increase above 2 times baseline, even if less than 2 times the ULN, may indicate early liver injury. Such elevations may warrant treatment suspension and prompt (48 to 72 hours) re-evaluation of liver test trends prior to reinitiating therapy with more frequent monitoring.

5.2 Tolvaptan for ADPKD Shared System REMS

JYNARQUE is available only through a restricted distribution program under a Risk Evaluation and Mitigation Strategy (REMS) called the Tolvaptan for ADPKD Shared System REMS, because of the risks of liver injury [see Warnings and Precautions (5.1)].

Notable requirements of the Tolvaptan for ADPKD Shared System REMS include the following:

- Prescribers must be certified by enrolling in the REMS program.
- Prescribers must inform patients receiving JYNARQUE about the risk of hepatotoxicity associated with its use and how to recognize the signs and symptoms of hepatotoxicity and the appropriate actions to take if it occurs.
- Patients must enroll in the REMS program and comply with ongoing monitoring requirements.
- Pharmacies must be certified by enrolling in the REMS program and must only dispense to patients who are authorized to receive JYNARQUE.

Further information, including a list of qualified pharmacies/distributors, is available at www.TolvaptanADPKDSharedREMS.com or by telephone at 1-866-244-9446.

5.3 Hypernatremia, Dehydration and Hypovolemia

JYNARQUE increases free water clearance and, as a result, may cause dehydration, hypovolemia and hypernatremia. Therefore, ensure abnormalities in sodium concentrations are corrected prior to initiation of therapy.

Instruct patients to drink water when thirsty, and throughout the day and night if awake. Monitor for weight loss, tachycardia and hypotension because they may signal dehydration.

In the two double-blind, placebo-controlled trials of patients with ADPKD, hypernatremia (defined as any serum sodium concentration >150 mEq/L) was observed in 4.0% versus 0.6% and 1.4% versus 0% of tolvaptan-treated versus placebo-treated patients, respectively. The rate of dehydration and hypovolemia in the two studies was 2.1% versus 0.7% and 2.3% versus 0.4% for tolvaptan-treated versus placebo-treated patients, respectively.

During JYNARQUE therapy, if serum sodium increases above normal range or the patient becomes hypovolemic or dehydrated and fluid intake cannot be increased, then suspend JYNARQUE until serum sodium, hydration status and volume status is within the normal range.

5.4 Co-Administration with Inhibitors of CYP3A

Concomitant use of JYNARQUE with drugs that are moderate or strong CYP3A inhibitors (e.g., ketoconazole, itraconazole, lopinavir/ritonavir, indinavir/ritonavir, ritonavir, and conivaptan) increases tolvaptan exposure [see Drug Interactions (7.1) and Clinical Pharmacology (12.3)]. Use with strong CYP3A inhibitors is contraindicated; dose reduction of JYNARQUE is recommended for patients while taking moderate CYP3A inhibitors [see Dosage and Administration (2.4) and Contraindications (4)].

6 ADVERSE REACTIONS

The following adverse reactions are discussed in more detail in other sections of the labeling:

- Serious Liver Injury [see Boxed Warning and Warnings and Precautions (5.1)]
- Hypernatremia, Dehydration and Hypovolemia [see Warnings and Precautions (5.3)]
- Drug Interactions with Inhibitors of CYP3A [see Warnings and Precautions (5.4)]

6.1 Clinical Trials Experience

Because clinical trials are conducted under widely varying conditions, adverse reaction rates observed in the clinical trials of a drug cannot be directly compared to rates in the clinical trials of another drug and may not reflect the rates observed in practice. JYNARQUE has been studied in over 3000 patients with ADPKD. Long-term, placebo-controlled safety information of JYNARQUE in ADPKD is principally derived from two trials where 1,413 subjects received tolvaptan and 1,098 received placebo for at least 12 months across both studies.

TEMPO 3:4: A Phase 3, Double-Blind, Placebo-Controlled, Randomized Trial in Early, Rapidly-Progressing ADPKD

The TEMPO 3:4 (NCT00428948) trial employed a two-arm, 2:1 randomization to tolvaptan or placebo, titrated to a maximally-tolerated total daily dose of 60 to 120 mg. A total of 961 subjects with rapidly progressing ADPKD were randomized to JYNARQUE. Of these, 742 (77%) subjects who were treated with JYNARQUE remained on treatment for at least 3 years. The average daily dose in these subjects was 96 mg daily.

Adverse events that led to discontinuation were reported for 15.4% (148/961) of subjects in the JYNARQUE group and 5.0% (24/483) of subjects in the placebo group. Aquaretic effects were the most common reasons for discontinuation of JYNARQUE. These included pollakiuria, polyuria, or nocturia in 63 (6.6%) subjects treated with JYNARQUE compared to 1 subject (0.2%) treated with placebo.

Table 2 lists the adverse reactions that occurred in at least 3% of ADPKD subjects treated with JYNARQUE and at least 1.5% more than on placebo.

Table 2: TEMPO 3:4, Treatment Emergent Adverse Reactions in ≥3% of JYNARQUE Treated Subjects with Risk Difference ≥1.5%, Randomized Period
Adverse Reaction | Tolvaptan (N=961) |  |  | Placebo (N=483)
Adverse Reaction | Number of Subjects | Proportion (%) [100× (Number of subjects with an adverse event/N)] | Annualized Rate [100× (Number of subjects with an adverse event/Total subject years of drug exposure)] | Number of Subjects | Proportion (%) | Annualized Rate
Increased urination [Increased urination includes micturition urgency, nocturia, pollakiuria, polyuria] | 668 | 69.5 | 28.6 | 135 | 28.0 | 10.3
Thirst [Thirst includes polydipsia and thirst] | 612 | 63.7 | 26.2 | 113 | 23.4 | 8.7
Dry mouth | 154 | 16.0 | 6.6 | 60 | 12.4 | 4.6
Fatigue | 131 | 13.6 | 5.6 | 47 | 9.7 | 3.6
Diarrhea | 128 | 13.3 | 5.5 | 53 | 11.0 | 4.1
Dizziness | 109 | 11.3 | 4.7 | 42 | 8.7 | 3.2
Dyspepsia | 76 | 7.9 | 3.3 | 16 | 3.3 | 1.2
Decreased appetite | 69 | 7.2 | 3.0 | 5 | 1.0 | 0.4
Abdominal distension | 47 | 4.9 | 2.0 | 16 | 3.3 | 1.2
Dry skin | 47 | 4.9 | 2.0 | 8 | 1.7 | 0.6
Rash | 40 | 4.2 | 1.7 | 9 | 1.9 | 0.7
Hyperuricemia | 37 | 3.9 | 1.6 | 9 | 1.9 | 0.7
Palpitations | 34 | 3.5 | 1.5 | 6 | 1.2 | 0.5

REPRISE: A Phase 3, Randomized-Withdrawal, Placebo-Controlled, Double-Blind, Trial in Late Stage 2 to Early Stage 4 ADPKD

The REPRISE (NCT02160145) trial employed a 5-week single-blind titration and run-in period for JYNARQUE prior to the randomized double-blind period. During the JYNARQUE titration and run-in period, 126 (8.4%) of the 1496 subjects discontinued the study, 52 (3.5%) were due to aquaretic effects and 10 (0.7%) were due to liver test findings. Because of this run-in design, the adverse reaction rates observed during the randomized period are not described.

Liver Injury

In the two double-blind, placebo-controlled trials, ALT elevations >3 times ULN were observed at an increased frequency with JYNARQUE compared with placebo (4.9% [80/1637] versus 1.1% [13/1166], respectively) within the first 18 months after initiating treatment and increases usually resolved within 1 to 4 months after discontinuing the drug.

6.2 Postmarketing Experience

The following adverse reactions have been identified during post-approval use of tolvaptan. Because these reactions are reported voluntarily from a population of uncertain size, it is not always possible to reliably estimate their frequency or establish a causal relationship to drug exposure.

Hepatobiliary Disorders: Liver failure requiring transplant

Immune System Disorders: Anaphylaxis

7 DRUG INTERACTIONS

7.1 CYP3A Inhibitors and Inducers

CYP3A Inhibitors

Tolvaptan's AUC was 5.4 times as large and Cmax was 3.5 times as large after co-administration of tolvaptan and 200 mg ketoconazole [see Warnings and Precautions (5.4) and Clinical Pharmacology (12.3)]. Larger doses of the strong CYP3A inhibitor would be expected to produce larger increases in tolvaptan exposure. Concomitant use of tolvaptan with strong CYP3A inhibitors is contraindicated [see Contraindications (4)].

Dose reduction of JYNARQUE is recommended for patients while taking moderate CYP3A inhibitors [see Dosage and Administration (2.4)]. Patients should avoid grapefruit juice beverages while taking JYNARQUE.

Strong CYP3A Inducers

Co-administration of JYNARQUE with strong CYP3A inducers reduces exposure to JYNARQUE [see Clinical Pharmacology (12.3)]. Avoid concomitant use of JYNARQUE with strong CYP3A inducers [see Dosage and Administration (2.4)].

7.2 V2-Receptor Agonist

As a V2-receptor antagonist, tolvaptan will interfere with the V2-agonist activity of desmopressin (dDAVP). Avoid concomitant use of JYNARQUE with a V2-agonist.

8 USE IN SPECIFIC POPULATIONS

8.1 Pregnancy

Risk Summary

Available data with JYNARQUE use in pregnant women are insufficient to determine if there is a drug associated risk of adverse developmental outcomes. In embryo-fetal development studies, pregnant rats and rabbits received oral tolvaptan during organogenesis. At maternally non-toxic doses, tolvaptan did not cause any developmental toxicity in rats or in rabbits at exposures approximately 4- and 1-times, respectively, the human exposure at the maximum recommended human dose (MRHD) of 90/30 mg. However, effects on embryo-fetal development occurred in both species at maternally toxic doses. In rats, reduced fetal weights and delayed fetal ossification occurred at 17 times the human exposure. In rabbits, increased abortions, embryo-fetal death, fetal microphthalmia, open eyelids, cleft palate, brachymelia and skeletal malformations occurred at approximately 3 times the human exposure (see Data). Advise pregnant women of the potential risk to the fetus.

The background risk of major birth defects and miscarriage for the indicated population is unknown. All pregnancies have a background risk of birth defect, loss, or other adverse outcomes. The estimated background risk of major birth defects and miscarriage in the U.S. general population is 2 to 4% and 15 to 20% of clinically recognized pregnancies, respectively.

Data

Animal Data

Oral administration of tolvaptan during the period of organogenesis in Sprague-Dawley rats produced no evidence of teratogenesis at doses up to 100 mg/kg/day. Lower body weights and delayed ossification were seen at 1000 mg/kg, which is approximately 17 times the human exposure at the 90/30 mg dose (AUC24h 6570 h∙ng/mL). The fetal effects are likely secondary to maternal toxicity (decreased food intake and low body weights). In a prenatal and postnatal study in rats, tolvaptan had no effect on physical development, reflex function, learning ability or reproductive performance at doses up to 1000 mg/kg/day.

In New Zealand White rabbits, placental transfer was demonstrated with Cmax values in the yolk sac fluid approximating 22.7% of the value in maternal rabbit serum. In embryo-fetal studies, teratogenicity (microphthalmia, embryo-fetal mortality, cleft palate, brachymelia and fused phalanx) was evident in rabbits at 1000 mg/kg (approximately 3 times the exposure at the 90/30 mg dose). Body weights and food consumption were lower in dams at all doses, equivalent to 0.6 to 3 times the human exposure at the 90/30 mg dose.

8.2 Lactation

Risk Summary

There are no data on the presence of tolvaptan in human milk, the effects on the breastfed infant, or the effects on milk production. Tolvaptan is present in rat milk. When a drug is present in animal milk, it is possible that the drug will be present in human milk, but relative levels may vary (see Data). Because of the potential for serious adverse reactions, including liver toxicity, electrolyte abnormalities (e.g., hypernatremia), hypotension, and volume depletion in breastfed infants, advise women not to breastfeed during treatment with JYNARQUE.

Data

In lactating rats administration of radiolabeled tolvaptan, lacteal radioactivity concentrations reached the highest level at 8 hours after administration and then decreased gradually with time with a half-life of 27.3 hours. The level of activity in milk ranged from 1.5- to 15.8-fold those in blood over the period of 72 hours post-dose. In a prenatal and postnatal study in rats, maternal toxicity was noted at 100 mg/kg/day or higher (≥4.4 times the human exposure at the 90/30 mg dose). Increased perinatal death and decreased body weight of the offspring were observed during the lactation period and after weaning at approximately 17.3 times the human exposure at the 90/30 mg dose.

8.4 Pediatric Use

Safety and effectiveness of JYNARQUE in pediatric patients have not been established.

8.5 Geriatric Use

Clinical studies of tolvaptan did not include sufficient numbers of subjects aged 65 years old and over to determine whether they respond differently from younger subjects. Other reported clinical experience has not identified differences in responses between the elderly and younger patients. In general, dose selection for an elderly patient should be cautious, usually starting at the low end of the dosing range, reflecting the greater frequency of decreased hepatic, renal, or cardiac function, and of concomitant disease or other drug therapy.

8.6 Use in Patients with Hepatic Impairment

Because of the risk of serious liver injury, use is contraindicated in patients with a history, signs or symptoms of significant liver impairment or injury. This contraindication does not apply to uncomplicated polycystic liver disease which was present in 60% and 66% of patients in TEMPO 3:4 and REPRISE, respectively. No specific exclusion for hepatic impairment was implemented in TEMPO 3:4. However, REPRISE excluded patients with ADPKD who had hepatic impairment or liver function abnormalities other than that expected for ADPKD with typical cystic liver disease [see Contraindications (4)].

8.7 Use in Patients with Renal Impairment

Efficacy studies included patients with normal and reduced renal function [see Clinical Studies (14)]. TEMPO 3:4 required patients to have an estimated creatinine clearance ≥60 mL/min, while REPRISE included patients with eGFRCKD-Epi 25 to 65 mL/min/1.73m^2.

10 OVERDOSAGE

Single oral doses up to 480 mg (4 times the maximum recommended daily dose) and multiple doses up to 300 mg once daily for 5 days have been well tolerated in trials in healthy subjects. There is no specific antidote for tolvaptan intoxication. The signs and symptoms of an acute overdose can be anticipated to be those of excessive pharmacologic effect: a rise in serum sodium concentration, polyuria, thirst, and dehydration/hypovolemia.

No mortality was observed in rats or dogs following single oral doses of 2000 mg/kg (maximum feasible dose). A single oral dose of 2000 mg/kg was lethal in mice, and symptoms of toxicity in affected mice included decreased locomotor activity, staggering gait, tremor and hypothermia.

In patients with suspected JYNARQUE overdosage, assessment of vital signs, electrolyte concentrations, ECG and fluid status is recommended. Continue replacement of water and electrolytes until aquaresis abates. Dialysis may not be effective in removing JYNARQUE because of its high binding affinity for human plasma protein (>98%).

11 DESCRIPTION

JYNARQUE contains tolvaptan, a selective vasopressin V2-receptor antagonist in immediate release tablets for oral administration available in 15 mg, 30 mg, 45 mg, 60 mg and 90 mg strengths. Tolvaptan is (±)-4'-[(7-chloro-2,3,4,5-tetrahydro-5-hydroxy-1H-1-benzazepin-1-yl) carbonyl]-o-tolu-m-toluidide. The empirical formula is C26H25ClN2O3. Molecular weight is 448.94. The chemical structure is:

Inactive ingredients include corn starch, hydroxypropyl cellulose, lactose monohydrate, low-substituted hydroxypropyl cellulose, magnesium stearate and microcrystalline cellulose and FD&C Blue No. 2 Aluminum Lake as colorant.

12 CLINICAL PHARMACOLOGY

12.1 Mechanism of Action

Tolvaptan is a selective vasopressin V2-receptor antagonist with an affinity for the V2-receptor that is 1.8 times that of native arginine vasopressin (AVP). Tolvaptan affinity for the V2-receptor is 29 times that for the V1a-receptor. Decreased binding of vasopressin to the V2-receptor in the kidney lowers adenylate cyclase activity resulting in a decrease in intracellular adenosine 3′, 5′-cyclic monophosphate (cAMP) concentrations. Decreased cAMP concentrations prevent aquaporin 2 containing vesicles from fusing with the plasma membrane, which in turn causes an increase in urine water excretion, an increase in free water clearance (aquaresis) and a decrease in urine osmolality. In human ADPKD cyst epithelial cells, tolvaptan inhibited AVP-stimulated in vitro cyst growth and chloride-dependent fluid secretion into cysts. In animal models, decreased cAMP concentrations were associated with decreases in the rate of growth of total kidney volume and the rate of formation and enlargement of kidney cysts. Tolvaptan metabolites have no or weak antagonist activity for human V2-receptors compared with tolvaptan.

12.2 Pharmacodynamics

In healthy subjects or patients with eGFRs as low as 10 mL/min/1.73m^2 receiving a single dose of tolvaptan, the onset of the aquaretic effects occurs within 1 to 2 hours post-dose. In healthy subjects, single doses of 60 mg and 90 mg produce a peak effect of about a 9 mL/min increase in urine excretion rate is observed between 4 and 8 hours post-dose. Higher doses of tolvaptan do not increase the peak effect in urine excretion rate but sustain the effect for a longer period of time.

Urine excretion rate returns to baseline within 24 hours following the maximum recommended 90 mg dose of tolvaptan.

Changes in free water clearance mirror the changes in urine excretion rate. Increased free water clearance causes an increase in serum sodium concentration unless fluid intake is increased to match urine output.

Increases in urine excretion rate and free water clearance are positively correlated with baseline glomerular filtration rate with increases in both values observed in patients with creatinine clearance as low as 15 mL/min.

With the recommended split-dose regimens, tolvaptan inhibits vasopressin from binding to the V2-receptor in the kidney for the entire day, as indicated by increased urine output and decreased urine osmolality. Following a 90/30 mg split-dose regimen in patients with eGFR >60 mL/min/1.73 m^2, the change in mean daily urine volume was about 4 L for a mean total daily volume of about 7 L. In patients with eGFR <30 mL/min/1.73 m^2, the mean change in daily urine volume was about 2 L for a total daily urine volume of about 5 L.

Plasma concentrations of native AVP may increase (avg. 2 to 9 pg/mL) with tolvaptan treatment and return to baseline levels when treatment is stopped.

During tolvaptan treatment, small changes in renal function are expected and the changes are independent of baseline renal function. Glomerular filtration rate is decreased about 6% to 10% and uric acid clearance is decreased about 20% to 25%. Percent changes in renal plasma flow are highly correlated to percent changes in GFR. These changes are reversed upon discontinuation of tolvaptan.

Cardiac Electrophysiology

No prolongation of the QT interval was observed with tolvaptan following multiple doses of 300 mg/day for 5 days.

12.3 Pharmacokinetics

In healthy subjects, the pharmacokinetics of tolvaptan after single doses of up to 480 mg and multiple doses up to 300 mg once daily have been studied. In ADPKD patients, single doses up to 120 mg and multiple split-doses up to 90/30 mg have been studied.

Absorption

In healthy subjects, peak concentrations of tolvaptan are observed between 2 and 4 hours post-dose. Peak concentrations increase less than dose proportionally with doses greater than 240 mg.

The absolute bioavailability of tolvaptan decreases with increasing doses. The absolute bioavailability of tolvaptan following an oral dose of 30 mg is 56% (range 42% to 80%).

Co-administration of 90 mg JYNARQUE with a high-fat meal (~1000 calories, of which 50% are from fat) doubles peak concentrations but has no effect on the AUC of tolvaptan; tolvaptan may be administered with or without food.

Distribution

Tolvaptan binds to both albumin and α1-acid glycoprotein and the overall protein binding is >98%; binding is not affected by disease state. The volume of distribution of tolvaptan is about 3 L/kg. The pharmacokinetic properties of tolvaptan are stereospecific, with a steady-state ratio of the S-(-) to the R-(+) enantiomer of about 3. When administered as multiple once-daily 300 mg doses to healthy subjects or as split-dose regimens to patients with ADPKD, tolvaptan's accumulation factor is <1.2. There is marked inter-subject variation in peak and average exposure to tolvaptan with a percent coefficient of variation ranging between 30% and 60%.

Metabolism and Elimination

Tolvaptan is metabolized almost exclusively by CYP3A. Fourteen metabolites have been identified in plasma, urine and feces; all but one were also metabolized by CYP3A and none are pharmacodynamically active. After oral administration of radiolabeled tolvaptan, tolvaptan was a minor component in plasma representing 3% of total plasma radioactivity; the oxobutyric acid metabolite was present at 52.5% of total plasma radioactivity with all other metabolites present at lower concentrations than tolvaptan. The oxobutyric acid metabolite shows a plasma half-life of ~180 h. About 40% of radioactivity was recovered in urine (<1% as unchanged tolvaptan) and 59% in feces (19% as unchanged tolvaptan). Following intravenous infusion, tolvaptan half-life is approximately 3 hours. Following single oral doses to healthy subjects, the estimated half-life of tolvaptan increases from 3 hours for a 15 mg dose to approximately 12 hours for 120 mg and higher doses due to more prolonged absorption of tolvaptan at higher doses; apparent clearance is approximately 4 mL/min/kg and does not appear to change with increasing dose.

Specific Populations

Age, Gender and Race

Age, gender and race have no effect on tolvaptan pharmacokinetics.

Hepatic Impairment

In studies involving patients with hepatic impairment (Child-Pugh class A-C), but without ADPKD; moderate (class A, B) or severe (class C) hepatic impairment decreases the clearance and increases the volume of distribution of tolvaptan.

Renal Impairment

In subjects with creatinine clearances ranging from 10 to 124 mL/min administered a single dose of 60 mg tolvaptan, the AUC and Cmax of plasma tolvaptan was increased 90% and 10%, respectively, for subjects with clearances of <30 mL/min compared to subjects with clearances >60 mL/min [see Use in Special Populations (8.7)].

In ADPKD patients with estimated creatinine clearance >60 mL/min, pharmacokinetics were similar to healthy subjects.

Drug Interaction Studies

Impact of Other Drugs on Tolvaptan

Strong CYP3A Inhibitors

Tolvaptan's Cmax and AUC were, respectively, 3.5 times and 5.4 times as high following ketoconazole 200 mg given one day prior to and concomitantly with 30 mg tolvaptan.

Moderate CYP3A4 Inhibitors

Fluconazole: Fluconazole 400 mg given one day prior and 200 mg given concomitantly produced an 80% and 200% increase in tolvaptan Cmax and AUC, respectively.

Grapefruit Juice: When 60 mg tolvaptan was taken with 240 mL regular strength grapefruit juice, tolvaptan Cmax and AUC increased 90% and 60%, respectively.

CYP3A Inducers

Rifampin: Rifampin 600 mg once daily for 7 days followed by a single 240 mg dose of tolvaptan decreased both tolvaptan Cmax and AUC about 85%.

Other Drugs

Co-administration of lovastatin, digoxin, furosemide, and hydrochlorothiazide with tolvaptan has no clinically relevant impact on the exposure to tolvaptan.

Impact of Tolvaptan on Other Drugs

CYP3A Substrates

Co-administration of lovastatin and tolvaptan increases the AUC of lovastatin and its active metabolite lovastatin-β hydroxy acid by 40% and 30%, respectively. These are non-clinically significant increases in exposure.

P-gp Substrates

Digoxin: Digoxin 0.25 mg was administered once daily for 12 days. Tolvaptan 60 mg, was co-administered once daily on Days 8 to 12. Digoxin Cmax and AUC were increased 30% and 20%, respectively.

Transporter Substrates

Tolvaptan is a substrate of P-gp and an inhibitor of P-gp and BCRP. The oxobutyric acid metabolite of tolvaptan is an inhibitor of OATP1B1 and OAT3. Co-administration of tolvaptan with rosuvastatin (BCRP substrate) did not have a clinically significant effect on rosuvastatin exposure. Rosuvastatin Cmax and AUCt increased 54% and 69%, respectively.

Administration of rosuvastatin (OATP1B1 substrate) or furosemide (OAT3 substrate) to healthy subjects with elevated oxobutyric acid metabolite plasma concentrations did not meaningfully alter the pharmacokinetics of rosuvastatin or furosemide.

Other Drugs

Co-administration of tolvaptan did not meaningfully alter the pharmacokinetics of warfarin, furosemide, hydrochlorothiazide, or amiodarone (or its active metabolite, desethylamiodarone).

13 NONCLINICAL TOXICOLOGY

13.1 Carcinogenesis, Mutagenesis, Impairment of Fertility

Carcinogenesis

The carcinogenic potential of JYNARQUE was assessed in 2-year carcinogenicity studies in mice and rats. Tolvaptan was not tumorigenic in male or female rats at doses up to 1000 mg/kg/day (1.9 to 5.1 times the human exposure at the 90/30 mg dose), in male mice at doses up to 60 mg/kg/day (0.4 times the human exposure at the 90/30 mg dose) and to female mice at doses up to 100 mg/kg/day (0.7 times the human exposure at the 90/30 mg dose).

Mutagenesis

Tolvaptan was not clastogenic in the in vitro chromosomal aberration test in Chinese hamster lung fibroblast cells or the in vivo rat micronucleus assay and was not mutagenic in the in vitro bacterial reverse mutation assay.

Impairment of fertility

In a fertility study in which male and female rats were administered tolvaptan orally at 100, 300 or 1000 mg/kg/day, altered estrous cycles due to prolongation of diestrus were observed in dams given 300 and 1000 mg/kg/day (9.7- and 17.3 times the human exposure at the 90/30 mg dose). Tolvaptan had no effect on copulation or fertility indices. There were also no effects on the incidences of early or late resorption, dead fetuses, pre- or post-implantation loss, external anomalies, or fetal body weights.

14 CLINICAL STUDIES

JYNARQUE was shown to slow the rate of decline in renal function in adult patients at risk of rapidly progressing ADPKD in two trials: TEMPO 3:4 in patients at earlier stages of disease and REPRISE in patients at later stages. The findings from these trials, when taken together, suggest that JYNARQUE slows the loss of renal function progressively through the course of the disease.

TEMPO 3:4: A Phase 3, Double-Blind, Placebo-Controlled, Randomized Trial in Early, Rapidly-Progressing ADPKD

In TEMPO 3:4 (NCT00428948), 1445 adult patients (age >18 years) with early (estimated creatinine clearance [eCrCl] ≥60 mL/min), rapidly-progressing (total kidney volume [TKV] ≥750 mL and age <51 years) ADPKD (diagnosed by modified Ravine criteria) were randomized 2:1 to treatment with tolvaptan or placebo. Patients were treated for up to 3 years; patients who discontinued medication prematurely were only required to attend clinic visits to assess renal function for up to 42 days after treatment withdrawal and to attend telephone visits at all scheduled visits for up to 36 months. Patients who completed treatment at the 3-year visit had treatment interrupted for 2 to 6 weeks to assess renal function post treatment. Patients received treatment twice a day (first dose on waking, second dose approximately 9 hours later). Patients were initiated on 45 mg/15 mg, and up-titrated weekly to 60 mg/30 mg and then to 90 mg/30 mg as tolerated. Patients were to maintain the highest tolerated dose for 3 years, but could interrupt, decrease and/or increase as clinical circumstances warranted within the range of titrated doses. All patients were encouraged to drink adequate water to avoid thirst or dehydration and before bedtime.

The primary endpoint was the intergroup difference for rate of change of TKV normalized as a percentage. The key secondary composite endpoint (ADPKD progression) was time to multiple clinical progression events of: 1) worsening kidney function (defined as a persistent 25% reduction in reciprocal serum creatinine during treatment from end of titration to last on-drug visit); 2) medically significant kidney pain (defined as requiring prescribed leave, last-resort analgesics, narcotic and anti-nociceptive, radiologic or surgical interventions); 3) worsening hypertension (defined as a persistent increase in blood pressure category or an increased anti-hypertensive prescription); 4) worsening albuminuria (defined as a persistent increase in albumin/creatinine ratio category).

At baseline, average estimated glomerular filtration rate (eGFR) was 82 mL/min/1.73 m^2 (CKD-Epidemiology formula) and mean TKV was 1692 mL (height adjusted 972 mL/m). Approximately 35% had an eGFR of 90 mL/min/1.73 m^2 or greater, 48% had an eGFR between 60 to 89 mL/min/1.73 m^2, 14% had an eGFR of 45 to 60 mL/min/1.73 m^2, and 3% had an eGFR of <45 mL/min/1.73 m^2. The subjects' mean age was 39 years, 48% were female, 84% were Caucasian, 13% were Asian, and 1.7% were Black or African-American. Approximately 80% had hypertension and approximately 71% were taking an agent that acts on the renin-angiotensin system. Of the 770 subjects who submitted to genetic analysis in TEMPO 3:4's open-label extension, 749 (97%) had an identifiable mutation in the PKD1 (656 or 88%), or PKD2 (93 or 12%) gene.

The trial met its prespecified primary endpoint of 3-year change in TKV (p<0.0001). The difference in TKV between treatment groups mostly developed within the first year, the earliest assessment, with little further difference in years two and three. In Years 4 and 5 during the TEMPO 3:4 extension trial, both groups received JYNARQUE and the difference between the groups in TKV was not maintained. Tolvaptan has little effect on kidney size beyond what accrues during the first year of treatment.

The relative rate of ADPKD-related events was decreased by 13.5% in tolvaptan-treated patients, (44 vs. 50 events per 100 person-years; hazard ratio, 0.87; 95% CI, 0.78 to 0.97; p=0.0095). As shown in the table below, the result of the key secondary composite endpoint was driven by effects on worsening kidney function and kidney pain events. In contrast, there was no effect of tolvaptan on either progression of hypertension or albuminuria. Few subjects in either arm required a radiologic or surgical intervention for kidney pain. Most kidney pain events reflected use of a medication to treat pain such as use of paracetamol, tricyclic antidepressants, narcotics and other non-narcotic agents.

Event | Tolvaptan |  | Placebo |  | Hazard Ratio, 95% CI
Event | Total Number of Events (Events per 100 person-years) | Number of Subjects with an Event (percentage) | Total Number of Events (Events per 100 person-years) | Number of Subjects with an Event (percentage) | Hazard Ratio, 95% CI
Composite | 1049 (43.9) | 572 (59.5) | 665 (50.0) | 341 (70.6) | 0.87 (0.78,0.97)
Worsening Kidney Function | 44 (1.9) | 42 (4.6) | 64 (4.8) | 61 (12.8) | 0.39 (0.26,0.57)
Kidney Pain | 113 (4.7) | 95 (9.9) | 97 (7.3) | 78 (16.2) | 0.64 (0.47,0.89)
Onset or Progression of Hypertension | 734 (30.7) | 426 (44.3) | 426 (32.1) | 244 (50.5) | 0.94 (0.81,1.09)
Worsening Albuminuria | 195 (8.2) | 195 (20.3) | 103 (7.8) | 101 (20.9) | 1.04 (0.84,1.28)

The third endpoint (kidney function slope) was assessed as slope of eGFR during treatment (from end of titration to last on-drug visit). The estimated difference in the annual rate of change in those who contributed to the analysis was 1.0 mL/min/1.73m^2/year with a 95% confidence interval of (0.6, 1.4). Of the subjects enrolled in the trial, 5% of subjects in the tolvaptan arm and 2% in the placebo arm either had missing baseline data or discontinued from treatment prior to the end of the titration visit and hence were excluded from the analysis. In the extension trial, eGFR differences produced by the third year of the TEMPO 3:4 trial were maintained over the next 2 years of JYNARQUE treatment.

The efficacy profile was generally consistent across subgroups of interest for this indication; few Black or African-American patients were enrolled in the trial.

REPRISE: A Phase 3, Double-Blind, Placebo-Controlled, Randomized Withdrawal Trial in Later-Stage ADPKD

REPRISE (NCT02160145) was a double-blind, placebo-controlled randomized withdrawal trial in adult patients (age 18 to 65 years) with chronic kidney disease (CKD) with an eGFR between 25 and 65 mL/min/1.73m^2 if younger than age 56 years, or eGFR between 25 and 44 mL/min/1.73m^2, plus eGFR decline >2.0 mL/min/1.73m^2/year if between age 56 to 65 years. Subjects were to be treated for 12 months; after completion of treatment, patients entered a 3-week follow-up period to assess renal function. The primary endpoint was the treatment difference in the change of eGFR from pre-treatment baseline to post-treatment follow-up, annualized by dividing by each subject's treatment duration.

Prior to randomization, patients were required to complete sequential single-blind run-in periods during which they received placebo for 1 week, followed by tolvaptan titration for 2 weeks, and then treatment with tolvaptan at the highest tolerated dose achieved during titration for 3 weeks. During the titration period, tolvaptan was up-titrated every 3 to 4 days from a daily oral dose of 30 mg/15 mg to 45 mg/15 mg, 60 mg/30 mg and up to a maximum dose of 90 mg/30 mg. Only patients who could tolerate the two highest doses of tolvaptan (60 mg/30 mg or 90 mg/30 mg) for the subsequent 3 weeks were randomized 1:1 to treatment with tolvaptan or placebo.

Patients were maintained on their highest tolerated dose for a period of 12 months but could interrupt, decrease and/or increase as clinical circumstances warranted within the range of titrated doses. All patients were encouraged to start drinking an adequate amount of water at screening and continuing through the end of the trial to avoid thirst or dehydration.

A total of 1519 subjects were enrolled in the study. Of these, 1370 subjects successfully completed the pre-randomization period and were randomized and treated during the 12-month double-blind period. Because 57 subjects did not complete the off-treatment follow-up period, 1313 subjects were included in the primary efficacy analysis.

For subjects randomized, the baseline, average estimated glomerular filtration rate (eGFR) was 41 mL/min/1.73 m^2 (CKD-Epidemiology formula) and historical TKV, available in 318 (23%) of subjects, averaged 2026 mL. Approximately 5%, 75% and 20% had an eGFR 60 mL/min/1.73 m^2 or greater, between 30 to 59 mL/min/1.73 m^2, and between 25 and 29 mL/min/1.73 m^2, respectively. The subjects' mean age was 47 years, 50% were female, 92% were Caucasian, 4% Black or African-American and 3% were Asian, 93% had hypertension, and 87% of subjects were taking antihypertensive agents affecting the angiotensin converting enzyme or receptor. Of the 115 (8%) of subjects who had prior genetic tests, only 54 (47%) knew their results with 48 (89%) of these having PKD1 and 6 (11%) having PKD2 mutations.

In the randomized period, the change of eGFR from pretreatment baseline to post-treatment follow-up was −2.3 mL/min/1.73 m^2/year with tolvaptan as compared with −3.6 mL/min/1.73 m^2/year with placebo, corresponding to a treatment effect of 1.3 mL/min/1.73 m^2/year (p <0.0001). The key secondary endpoint (eGFR slope in ml/min/1.73 m^2/year assessed using a linear mixed effect model of annualized eGFR (CKD-EPI)) showed a difference between treatment groups of 1.0 ml/min/ m^2/year that was also statistically significant (p <0.0001).

The efficacy profile was generally consistent across subgroups of interest for this indication; few Black or African-American patients were enrolled in the trial.

16 HOW SUPPLIED/STORAGE AND HANDLING

How Supplied

All JYNARQUE (tolvaptan) tablets are non-scored, blue, shallow-convex, debossed with "OTSUKA" and the tablet strength (mg) on one side and supplied as follows:

15 mg tablets are triangular, 30 mg tablets are round, 45 mg tablets are square, 60 mg tablets are rectangular, and 90 mg tablets are pentagonal.

Morning and Afternoon Doses | NDC
Morning and Afternoon Doses | 7‑Day Blister Card (Containing 14 Tablets) | 28‑Day Carton (4 Blister Cards Containing a Total of 56 Tablets)
15 mg and 15 mg | 59148-079-07 | 59148-079-28
30 mg and 15 mg | 59148-080-07 | 59148-080-28
45 mg and 15 mg | 59148-087-07 | 59148-087-28
60 mg and 30 mg | 59148-088-07 | 59148-088-28
90 mg and 30 mg | 59148-089-07 | 59148-089-28

30 Count Bottles | NDC
15 mg | 59148-082-13
30 mg | 59148-083-13

Storage and Handling

Store at 20°C to 25°C (68°F to 77°F), excursions permitted between 15°C and 30°C (59°F to 86°F) [see USP controlled Room Temperature].

17 PATIENT COUNSELING INFORMATION

As part of patient counseling, healthcare providers must review the JYNARQUE Medication Guide with every patient [see Medication Guide].

Serious Liver Injury

Advise patients that blood testing is required before starting JYNARQUE, at 2 weeks and 4 weeks after initiation, then monthly during the first 18 months of therapy and every 3 months thereafter as a requirement to reduce the risk of serious liver injury [see Boxed Warning and Warnings and Precautions (5.1)].

Advise patients to immediately stop taking JYNARQUE and notify their healthcare provider if they have symptoms or signs (e.g., abnormal transaminase elevations) of hepatic injury (such as fatigue, anorexia, nausea, right upper abdominal discomfort or tenderness, vomiting, fever, rash, pruritus, icterus, dark urine or jaundice) [see Warnings and Precautions (5.1)].

Tolvaptan for ADPKD Shared System REMS

Advise patients that JYNARQUE is only available through a restricted program called the Tolvaptan for ADPKD Shared System REMS [see Warnings and Precautions (5.2)]. Inform the patient of the following notable requirement:

- Patients must enroll in the program and comply with ongoing monitoring requirements [see Warnings and Precautions (5.2)]

Advise patients that JYNARQUE is only available only through restricted distribution from certified specialty pharmacies participating in the Tolvaptan for ADPKD Shared System REMS. Therefore, provide patients with the telephone number and web site for information on how to obtain the product [see Warnings and Precautions (5.2)].

Hypernatremia, Dehydration and Hypovolemia

Advise patients to drink water to avoid thirst, throughout the day and night. Patients should stop taking JYNARQUE and notify their healthcare provider if they have symptoms or signs of sodium imbalance or dehydration (e.g., dizziness, fainting, weight loss, palpitations, confusion, weakness, gait instability) [see Warnings and Precautions (5.3)]. Advise the patient that if they cannot drink enough water for any reason (no access to water, cannot sense thirst, unable to maintain hydration due to vomiting, diarrhea) they should stop taking JYNARQUE and inform their health care provider right away [see Warnings and Precautions (5.3)].

Pregnancy

Advise pregnant women of the potential risk to a fetus. Advise females of reproductive potential to inform their prescriber of a known or suspected pregnancy [see Use in Specific Populations (8.1)].

Lactation

Advise women not to breastfeed during treatment with JYNARQUE [see Use in Specific Populations (8.2)].

Manufactured by Otsuka Pharmaceutical Co., Ltd., Tokyo, 101-8535 Japan

Distributed and marketed by Otsuka America Pharmaceutical, Inc., Rockville, MD 20850 USA

JYNARQUE is a registered trademark of Otsuka Pharmaceutical Co., Ltd., Tokyo, 101-8535 Japan

©2025, Otsuka Pharmaceutical Co., Ltd., Tokyo, 101-8535 Japan

MEDICATION GUIDE
JYNARQUE® (jin-AR-kew)
(tolvaptan)
Tablets

What is the most important information I should know about JYNARQUE?
JYNARQUE can cause serious side effects, including:

- Serious liver problems. JYNARQUE can cause serious liver problems that can lead to the need for a liver transplant or can lead to death. Stop taking JYNARQUE and call your healthcare provider right away if you get any of the following symptoms:

- feeling tired
- loss of appetite
- nausea
- right upper stomach (abdomen) pain or tenderness
- vomiting

- fever
- rash
- itching
- yellowing of the skin and white part of the eye (jaundice)
- dark urine

To help reduce your risk of liver problems, your healthcare provider will do a blood test to check your liver:

- before you start taking JYNARQUE
- at 2 weeks and 4 weeks after you start treatment with JYNARQUE
- then monthly for 18 months during treatment with JYNARQUE
- and every 3 months from then on

It is important to stay under the care of your healthcare provider during treatment with JYNARQUE.
Because of the risk of serious liver problems JYNARQUE is only available through a restricted distribution program called the Tolvaptan for ADPKD Shared System REMS.

- Before you start treatment with JYNARQUE, you must enroll in the Tolvaptan for ADPKD Shared System REMS. Talk to your healthcare provider about how to enroll in the program.
- JYNARQUE can only be dispensed by a certified pharmacy that participates in the Tolvaptan for ADPKD Shared System REMS. Your healthcare provider can give you information on how to find a certified pharmacy.

What is JYNARQUE?
JYNARQUE is a prescription medicine used to slow kidney function decline in adults who are at risk of rapidly progressing autosomal dominant polycystic kidney disease (ADPKD).
It is not known if JYNARQUE is safe and effective in children.

Do not take JYNARQUE if you:

- have a history of liver problems or have signs or symptoms of liver problems, excluding polycystic liver disease.
- cannot feel if you are thirsty or cannot replace fluids by drinking.
- have been told that the amount of sodium (salt) in your blood is too high or too low.
- are dehydrated.
- are allergic to tolvaptan or any of the ingredients in JYNARQUE. See the end of this Medication Guide for a complete list of ingredients in JYNARQUE.
- are unable to urinate.

Before taking JYNARQUE, tell your healthcare provider about all your medical conditions, including if you:

- have a history of sodium levels that are too low.
- are pregnant or plan to become pregnant. It is not known if tolvaptan will harm your unborn baby. Tell your healthcare provider if you become pregnant or think that you may be pregnant.
- are breast-feeding or plan to breastfeed. It is not known if tolvaptan passes into your breast milk. Do not breastfeed during treatment with JYNARQUE. Talk to your healthcare provider about the best way to feed your baby during this time.

Tell your healthcare provider about all the medicines you take including prescription medicines, over-the-counter medicines, vitamins and herbal supplements.

- Taking JYNARQUE with certain medicines could cause you to have too much tolvaptan in your blood. JYNARQUE should not be taken with certain medications. Your healthcare provider can tell you if it is safe to take JYNARQUE with other medicines.
- Do not start taking a new medicine without talking to your healthcare provider.
- Keep a list of your medicines to show your healthcare provider and pharmacist.

How should I take JYNARQUE?

- Take JYNARQUE exactly as your healthcare provider tells you to.
- Take JYNARQUE orally two times each day. Take the first dose of JYNARQUE when you wake up and take the second dose 8 hours later.
- Be sure to drink enough water so that you will not get thirsty or become dehydrated.
- If you miss a dose of JYNARQUE, take the next dose at your regular time.
- If you take too much JYNARQUE, call your healthcare provider or go to the nearest hospital emergency room right away.

What should I avoid while taking JYNARQUE?

- Do not drink grapefruit juice during treatment with JYNARQUE. This could cause you to have too much tolvaptan in your blood.

What are the possible side effects of JYNARQUE?
JYNARQUE may cause serious side effects, including:
See "What is the most important information I should know about JYNARQUE?"

- Too much sodium in your blood (hypernatremia) and loss of too much body fluid (dehydration). In some cases, dehydration can lead to extreme loss of body fluid called hypovolemia. You should drink water when you are thirsty and throughout the day and night. Stop taking JYNARQUE and call your healthcare provider if you cannot drink enough water for any reason, such as not having access to water, or vomiting or diarrhea. Tell your healthcare provider if you get any of the following symptoms:
  - dizziness
  - fainting
  - weight loss
  - a change in the way your heart beats
  - feel confused or weak

The most common side effects of JYNARQUE include:

- thirst and drinking more fluid than normal
- making large amounts of urine, urinating often and urinating at night

These are not all the possible side effects of JYNARQUE.
Call your doctor for medical advice about side effects. You may report side effects to FDA at 1-800-FDA-1088.

How should I store JYNARQUE?
JYNARQUE comes in a child-resistant package. Store JYNARQUE between 68°F to 77°F (20°C to 25°C).
Keep JYNARQUE and all medicines out of the reach of children.

General information about the safe and effective use of JYNARQUE.
Medicines are sometimes prescribed for purposes other than those listed in a Medication Guide. Do not use JYNARQUE for a condition for which it was not prescribed. Do not give JYNARQUE to other people, even if they have the same symptoms you have. It may harm them.

What are the ingredients in JYNARQUE?
Active ingredient: tolvaptan
Inactive ingredients: corn starch, hydroxypropyl cellulose, lactose monohydrate, low-substituted hydroxypropyl cellulose, magnesium stearate and microcrystalline cellulose, and FD&C Blue no. 2 Aluminum Lake as colorant.

Manufactured by Otsuka Pharmaceutical Co., Ltd., Tokyo, 101-8535 Japan
Distributed and marketed by Otsuka America Pharmaceutical, Inc., Rockville, MD 20850 USA
JYNARQUE is a registered trademark of Otsuka Pharmaceutical Co., Ltd., Tokyo, 101-8535 Japan
©2025, Otsuka Pharmaceutical Co., Ltd., Tokyo, 101-8535 Japan
For more information about JYNARQUE, go to www.TolvaptanADPKDSharedREMS.com or call 1-866-244-9446.

This Medication Guide has been approved by the U.S. Food and Drug Administration.

Revised: 3/2025

PRINCIPAL DISPLAY PANEL - Kit Carton - 45 mg and 15 mg

56 Tablets
Monthly Carton contains
4 child resistant Weekly Packs.
Each Weekly Pack contains 1 blister card with
14 tablets (7 x 45 mg tablets and 7 x 15 mg tablets).

NDC 59148-087-28
Rx only

JYNARQUE®
(tolvaptan) tablets

45 mg
per tablet
and
15 mg
per tablet

DISPENSE THE ENCLOSED MEDICATION GUIDE TO EACH PATIENT

PRINCIPAL DISPLAY PANEL - Kit Carton - 60 mg and 30 mg

56 Tablets
Monthly Carton contains
4 child resistant Weekly Packs.
Each Weekly Pack contains 1 blister card with
14 tablets (7 x 60 mg tablets and 7 x 30 mg tablets).

NDC 59148-088-28
Rx only

JYNARQUE®
(tolvaptan) tablets

60 mg
per tablet
and
30 mg
per tablet

DISPENSE THE ENCLOSED MEDICATION GUIDE TO EACH PATIENT

PRINCIPAL DISPLAY PANEL - Kit Carton - 90 mg and 30 mg

56 Tablets
Monthly Carton contains
4 child resistant Weekly Packs.
Each Weekly Pack contains 1 blister card with
14 tablets (7 x 90 mg tablets and 7 x 30 mg tablets).

NDC 59148-089-28
Rx only

JYNARQUE®
(tolvaptan) tablets

90 mg
per tablet
and
30 mg
per tablet

DISPENSE THE ENCLOSED MEDICATION GUIDE TO EACH PATIENT

PRINCIPAL DISPLAY PANEL - 15 mg Tablet Label

NDC 59148-082-13

Rx only

JYNARQUE®
(tolvaptan) tablets

15 mg

DISPENSE THE ENCLOSED MEDICATION
GUIDE TO EACH PATIENT

30 tablets

PRINCIPAL DISPLAY PANEL - 30 mg Tablet Label

NDC 59148-083-13

Rx only

JYNARQUE®
(tolvaptan) tablets

30 mg

DISPENSE THE ENCLOSED MEDICATION
GUIDE TO EACH PATIENT

30 tablets

PRINCIPAL DISPLAY PANEL - 15 mg Tablet Bottle Carton

NDC 59148-082-13
Rx only

JYNARQUE®
(tolvaptan) tablets

15 mg

DISPENSE THE ENCLOSED MEDICATION
GUIDE TO EACH PATIENT

30 tablets

PRINCIPAL DISPLAY PANEL - 30 mg Tablet Bottle Carton

NDC 59148-083-13
Rx only

JYNARQUE®
(tolvaptan) tablets

30 mg

DISPENSE THE ENCLOSED MEDICATION
GUIDE TO EACH PATIENT

30 tablets

PRINCIPAL DISPLAY PANEL - 45-15 mg Sleeve

1
Press here
to open

14 Tablets
Weekly Pack contains
1 blister card with 14 tablets
(7 x 45 mg tablets and 7 x 15 mg tablets).

NDC 59148-087-07
Rx only

JYNARQUE®
(tolvaptan) tablets

45 mg
per tablet
and
15 mg
per tablet

Instructions to the right

1. Using thumbnail, press and hold down perforated button.
2. While holding button down, pull out foil package.
3. Push tablet through foil.
4. Push weekly pack into carton.

DISPENSE THE ENCLOSED
MEDICATION GUIDE
TO EACH PATIENT

2
PULL HERE

PRINCIPAL DISPLAY PANEL - 60-30 mg Sleeve

1
Press here
to open

14 Tablets
Weekly Pack contains
1 blister card with 14 tablets
(7 x 60 mg tablets and 7 x 30 mg tablets).

NDC 59148-088-07
Rx only

JYNARQUE®
(tolvaptan) tablets

60 mg
per tablet
and
30 mg
per tablet

Instructions to the right

1. Using thumbnail, press and hold down perforated button.
2. While holding button down, pull out foil package.
3. Push tablet through foil.
4. Push weekly pack into carton.

DISPENSE THE ENCLOSED
MEDICATION GUIDE
TO EACH PATIENT

2
PULL HERE

PRINCIPAL DISPLAY PANEL - 90-30 mg Sleeve

1
Press here
to open

14 Tablets
Weekly Pack contains
1 blister card with 14 tablets
(7 x 90 mg tablets and 7 x 30 mg tablets).

NDC 59148-089-07
Rx only

JYNARQUE®
(tolvaptan) tablets

90 mg
per tablet
and
30 mg
per tablet

Instructions to the right

1. Using thumbnail, press and hold down perforated button.
2. While holding button down, pull out foil package.
3. Push tablet through foil.
4. Push weekly pack into carton.

DISPENSE THE ENCLOSED
MEDICATION GUIDE
TO EACH PATIENT

2
PULL HERE

PRINCIPAL DISPLAY PANEL - 15-15 mg Sleeve

1
Press here
to open

14 Tablets
Weekly Pack contains
1 blister card with 14 tablets
(14 x 15 mg tablets).

NDC 59148-079-07
Rx only

JYNARQUE®
(tolvaptan) tablets

15 mg
per tablet
and
15 mg
per tablet

Instructions to the right

1. Using thumbnail, press and hold down perforated button.
2. While holding button down, pull out foil package.
3. Push tablet through foil.
4. Push weekly pack into carton.

DISPENSE THE ENCLOSED
MEDICATION GUIDE
TO EACH PATIENT

2
PULL HERE

PRINCIPAL DISPLAY PANEL - 30-15 mg Sleeve

1
Press here
to open

14 Tablets
Weekly Pack contains
1 blister card with 14 tablets
(7 x 30 mg tablets and 7 x 15 mg tablets).

NDC 59148-080-07
Rx only

JYNARQUE®
(tolvaptan) tablets

30 mg
per tablet
and
15 mg
per tablet

Instructions to the right

1. Using thumbnail, press and hold down perforated button.
2. While holding button down, pull out foil package.
3. Push tablet through foil.
4. Push weekly pack into carton.

DISPENSE THE ENCLOSED
MEDICATION GUIDE
TO EACH PATIENT

2
PULL HERE

PRINCIPAL DISPLAY PANEL - Kit Carton - 30 mg and 15 mg

56 Tablets
Monthly Carton contains
4 child resistant Weekly Packs.
Each Weekly Pack contains 1 blister card with
14 tablets (7 x 30 mg tablets and 7 x 15 mg tablets).

NDC 59148-080-28
Rx only

JYNARQUE®
(tolvaptan) tablets

30 mg
per tablet
and
15 mg
per tablet

DISPENSE THE ENCLOSED MEDICATION GUIDE TO EACH PATIENT

PRINCIPAL DISPLAY PANEL - Kit Carton - 15 mg and 15 mg

56 Tablets
Monthly Carton contains
4 child resistant Weekly Packs.
Each Weekly Pack contains 1 blister card with
14 tablets (14 x 15 mg tablets).

NDC 59148-079-28
Rx only

JYNARQUE®
(tolvaptan) tablets

15 mg
per tablet
and
15 mg
per tablet

DISPENSE THE ENCLOSED MEDICATION GUIDE TO EACH PATIENT